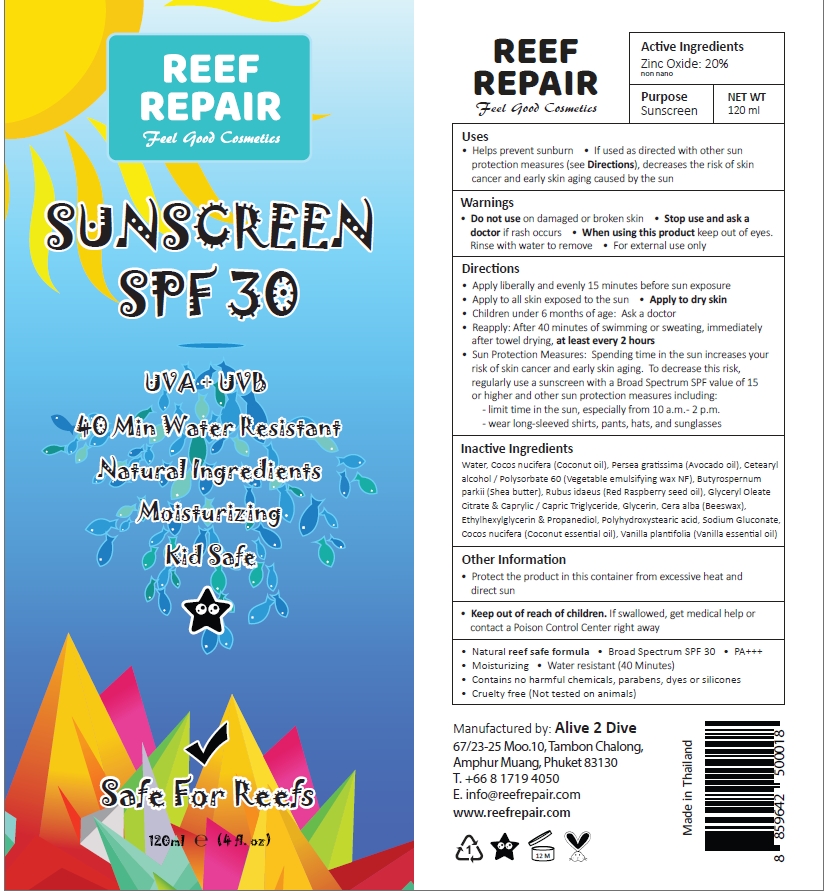 DRUG LABEL: Reef Repair SPF 30
NDC: 73541-001 | Form: CREAM
Manufacturer: Alive 2 Dive Company Limited
Category: otc | Type: HUMAN OTC DRUG LABEL
Date: 20240407

ACTIVE INGREDIENTS: ZINC OXIDE 20 g/100 mL
INACTIVE INGREDIENTS: POLYHYDROXYSTEARIC ACID (2300 MW); VANILLA PLANIFOLIA OIL; WHITE WAX; ETHYLHEXYLGLYCERIN; MEDIUM-CHAIN TRIGLYCERIDES; COCONUT OIL; AVOCADO OIL; SODIUM GLUCONATE; CETOSTEARYL ALCOHOL; POLYSORBATE 60; SHEA BUTTER; RASPBERRY SEED OIL; GLYCERYL MONOOLEATE CITRATE; GLYCERIN; PROPANEDIOL

Reef Repair Suncream SPF 30+

Active ingredient

Zinc Oxide, 20%

Purpose

Sunscreen

Uses

- Helps prevent sunburn
- If used as directed with other sun protection measures (see Directions), decrease the risk of skin cancer and early skin aging caused by the sun

Warnings

For external use only

keep out of reach of children

If swallowed, get medical help or contact a Poison Control Center right away.

Do not use on damaged or broken skin

Stop use and ask a doctor if rash occurs

When using this product keep out of eyes. Rinse with water to remove

Directions

- Apply liberally and evenly to dry skin 15 minutes before sun exposure
- Apply to all skin exposed to the sun
- Apply to dry skin
- Children under 6 months of age: Ask a doctor
- Reapply: aAfter 80 minutes of swimming or sweating, immediately after towel drying, at least every 2 hours
- Sun Proctection Measures: Spending time in the sun increases your risk of skin cance and early skin aging. To decrease this risk, regularly use a sunscreen with a Broas Spectrum SPF calue of 15 or higher and other sun protection measures including:-limit time in the sun, especially from 10 a.m.-2 p.m.

-wear long-sleeved shirts, pants, hats, and sunglasses

Inactive ingredients

Aqua, Cocos nuciera (Coconut oil), Persea gratissma (Avocado oil), Cetearyl alcohol / Polysorbate 60 (Vegatable emulsifying wax NF), Butyrospernum parkii (Shea butter), Rubus idaeus (Red Raspberry seed oil), Glyceryl Oleate Citrate & Caprylic / Capric Triglyceride, Glycerin, Cera alba (Beeswax), Ethylhexylglycerin & Propanediol, Polyhydoxystearic acid, Sodium Gluconate, Cocos nucifera (Coconut essential oil), Vanilla plantifolia (Vanilla essential oil)

Other Information

- Protect the product in this container from excessive heat and direct sun
- 100% biodegradable non-toxic, reef safe formula
- Contains no harmful chemicals, parabens or silicones
- Broad Spectrum SPF 30+
- PA+++
- Moisturizing
- Cruetly free (Not tested on animals)
- Water resistant (80 Minutes)